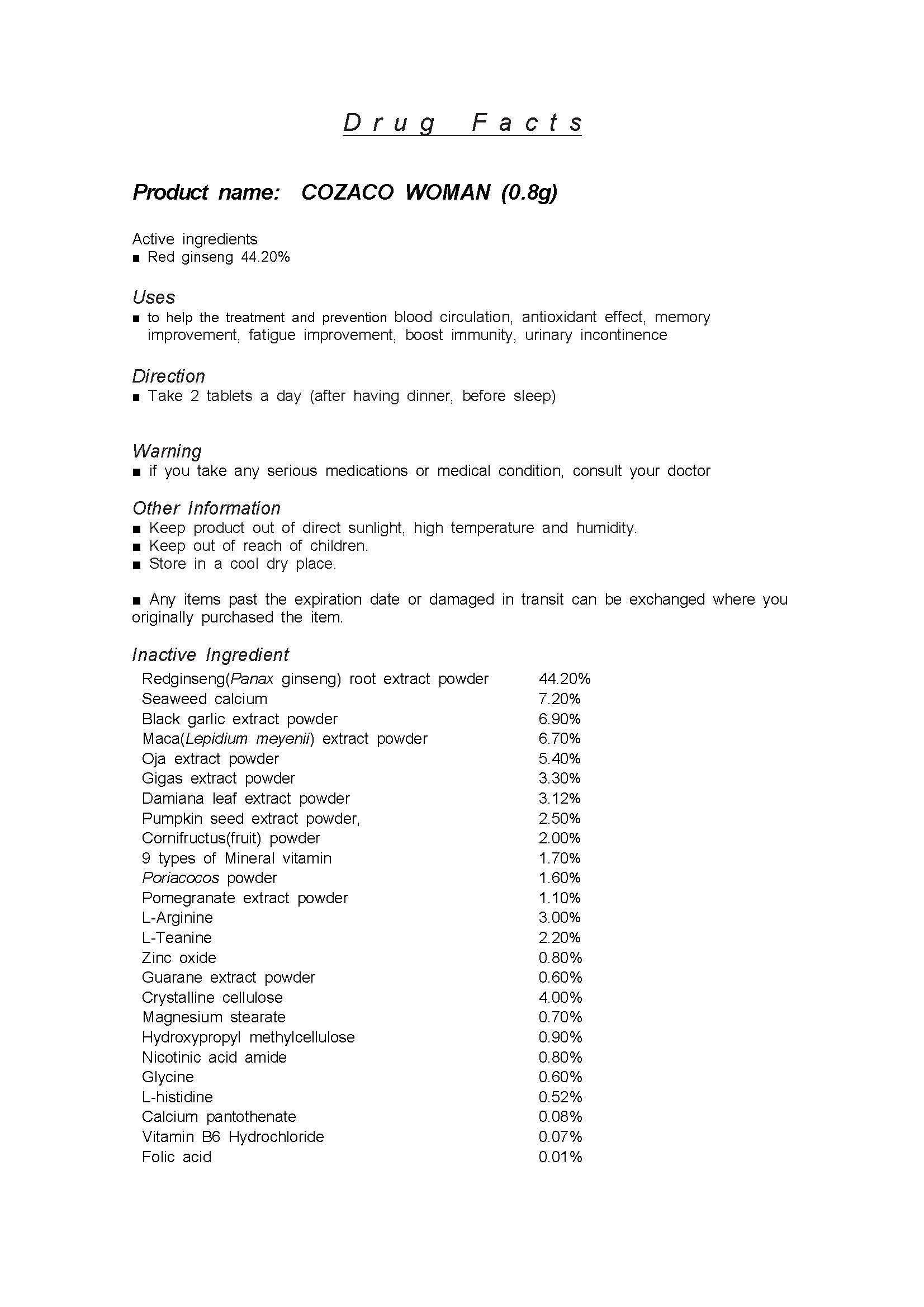 DRUG LABEL: COZACO WOMAN
NDC: 81651-0002 | Form: TABLET
Manufacturer: Kone Bio Logics Co., Ltd.
Category: otc | Type: HUMAN OTC DRUG LABEL
Date: 20220110

ACTIVE INGREDIENTS: PANAX GINSENG ROOT OIL 44.2 1/1 1
INACTIVE INGREDIENTS: GARLIC OIL

ACTIVE INGREDIENT

Red ginseng

INACTIVE INGREDIENT

Seaweed calcium

Black garlic extract powder

Maca(Lepidium meyenii) extract powder

Oja extract powder

Gigas extract powder

Damiana leaf extract powder

Pumpkin seed extract powder,

Cornifructus(fruit) powder

9 types of Mineral vitamin

Poriacocos powder

Pomegranate extract powder

L-Arginine

L-Teanine

Zinc oxide

Guarane extract powder

Crystalline cellulose

Magnesium stearate

Hydroxypropyl methylcellulose

Nicotinic acid amide

Glycine

L-histidine

Calcium pantothenate

Vitamin B6 Hydrochloride

Folic acid

PURPOSE

blood circulation, antioxidant effect, memory improvement, fatigue improvement, boost immunity, urinary incontinence

KEEP OUT OF REACH OF CHILDREN

WARNING

Please check product ingredients if you have any allergies before taking.

Please be careful during open the product package.

Keep product out of direct sunlight, high temperature and humidity.

Store in a cool dry place.

Any items past the expiration date or damaged in transit can be exchanged where you originally purchased the item.

consult your doctor if any abnormal symptoms occur

USES

for oral use only

INDICATION & USAGE SECTION

Take 2 tablets a day (after having dinner, before sleep)